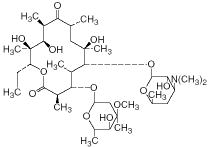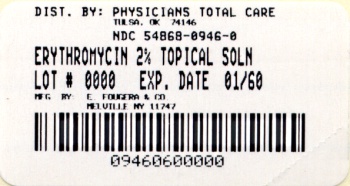 DRUG LABEL: Erythromycin
NDC: 54868-0946 | Form: SOLUTION
Manufacturer: Physicians Total Care, Inc.
Category: prescription | Type: HUMAN PRESCRIPTION DRUG LABEL
Date: 20100729

ACTIVE INGREDIENTS: ERYTHROMYCIN 20 mg/1 1
INACTIVE INGREDIENTS: ALCOHOL 71.5 mg/1 1; PROPYLENE GLYCOL; ANHYDROUS CITRIC ACID

For Dermatologic Use Only
Not for Ophthalmic Use

Rx only

DESCRIPTION

Erythromycin Pledgets, USP contains erythromycin ((3R*,4S*,5S*,6R*,7R*,9R*,11R*,12R*,13S*,14R*)-4-[(2,6-Dideoxy-3-C-methyl-3-O-methyl-α-⌊-ribo-hexopyranosyl)-oxy]-14-ethyl-7,12,13-trihydroxy 3,5,7,9,11,13-hexamethyl-6-[[3,4,6-trideoxy-3-(dimethylamino)-β-d-xylo-hexopyranosyl]oxy]oxacyclotetradecane-2,10-dione), for topical dermatologic use. Erythromycin is a macrolide antibiotic produced from a strain of Saccharopolyspora erythraea (formerly Streptomyces erythreus).

It is a base and readily forms salts with acids. Chemically, erythromycin is C37H67NO13. It has the following structural formula:

Erythromycin has the molecular weight of 733.94

It is a white powder, is freely soluble in alcohols, acetone, chloroform, acetonitrile, ethyl acetate, and moderately soluble in ether, ethylene dichloride and amyl acetate. Erythromycin pledgets, USP are absorbent pads impregnated with Erythromycin Topical Solution 2%. Each pledget contains 1 mL of Erythromycin Topical Solution 2% and each 1 mL of Erythromycin Topical Solution 2% contains 20 mg of erythromycin base in a vehicle consisting of alcohol (71.5% v/v) and propylene glycol. May contain anhydrous citric acid and/or alcohol to adjust pH.

CLINICAL PHARMACOLOGY

The exact mechanism by which erythromycin reduces lesions of acne vulgaris is not fully known: however, the effect appears to be due in part to the antibacterial activity of the drug.

Microbiology: Erythromycin acts by inhibition of protein synthesis in susceptible organisms by reversibly binding to 50 S ribosomal subunits, thereby inhibiting translocation of aminoacyl transfer-RNA and inhibiting polypeptide synthesis. Antagonism has been demonstrated in vitro between erythromycin, lincomycin, chloramphenicol, and clindamycin.

INDICATIONS AND USAGE

Erythromycin pledgets, USP are indicated for the topical treatment of acne vulgaris.

CONTRAINDICATIONS

Erythromycin pledgets, USP are contraindicated in those individuals who have shown hypersensitivity to any of its components.

WARNINGS

Pseudomembranous colitis has been reported with nearly all antibacterial agents, including erythromycin, and may range in severity from mild to life-threatening. Therefore, it is important to consider this diagnosis in patients who present with diarrhea subsequent to the administration of antibacterial agents.

Treatment with antibacterial agents alters the normal flora of the colon and may permit overgrowth of clostridia. Studies indicate that a toxin produced by Clostridium difficile is one primary cause of ``antibiotic-associated colitis′′.

After the diagnosis of pseudomembranous colitis has been established, therapeutic measures should be initiated. Mild cases of pseudomembranous colitis usually respond to drug discontinuation alone.

In moderate to severe cases, consideration should be given to management with fluids and electrolytes, protein supplementation and treatment with an antibacterial drug clinically effective against C. difficile colitis.

PRECAUTIONS

General: For topical use only; not for ophthalmic use. Concomitant topical acne therapy should be used with caution because a possible cumulative irritancy effect may occur, especially with the use of peeling, desquamating or abrasive agents.The use of antibiotic agents may be associated with the overgrowth of antibiotic-resistant organisms. If this occurs, discontinue use and take appropriate measures.

Avoid contact with eyes and all mucous membranes.

Information for Patients: Patients using erythromycin pledgets, USP should receive the following information and instructions:

1. This medication is to be used as directed by the physician. It is for external use only. Avoid contact with the eyes, nose, mouth, and all mucous membranes.
2. This medication should not be used for any disorder other than that for which it was prescribed.
3. Patients should not use any other topical acne medication unless otherwise directed by their physician.
4. Patients should report to their physician any signs of local adverse reactions.

Carcinogenesis, mutagenesis, impairment of fertility: No animal studies have been performed to evaluate the carcinogenic and mutagenic potential or effects on fertility of topical erythromycin. However, long-term (2 year) oral studies in rats with erythromycin ethylsuccinate and erythromycin base did not provide evidence of tumorigenicity. There was no apparent effect on male or female fertility in rats fed erythromycin (base) at levels up to 0.25% of diet.

Pregnancy: Teratogenic effects: Pregnancy Category B. There was no evidence of teratogenicity or any other adverse effect on reproduction in female rats fed erythromycin base (up to 0.25% diet) prior to and during mating, during gestation and through weaning of two successive litters.

There are, however, no adequate and well-controlled studies in pregnant women. Because animal reproduction studies are not always predictive of human response, this drug should be used in pregnancy only if clearly needed. Erythromycin has been reported to cross the placental barrier in humans, but fetal plasma Ievels are generally low.

Nursing Mothers: It is not known whether erythromycin is excreted in human milk after topical application. However, erythromycin is excreted in human milk following oral and parenteral erythromycin administration. Therefore, caution should be exercised when erythromycin is administered to a nursing woman.

Pediatric Use: Safety and effectiveness of this product in pediatric patients have not been established.

ADVERSE REACTIONS

The following local adverse reactions have been reported occasionally: peeling, dryness, itching, erythema, and oiliness. Irritation of the eyes and tenderness of the skin have also been reported with topical use of erythromycin. Generalized urticarial reactions, possibly related to the use of erythromycin, which required systemic steroid therapy have been reported.

DOSAGE AND ADMINISTRATION

Erythromycin pledgets, USP should be rubbed over the affected area twice a day after the skin is thoroughly washed with warm water and soap and patted dry. Acne lesions on the face, neck, shoulder, chest, and back may be treated in this manner. Additional pledgets may be used, if needed. Each pledget should be used once and discarded.

HOW SUPPLIED

Each pledget is filled to contain 1 mL of Erythromycin Topical Solution USP 2%. Each mL of Erythromycin Topical Solution USP 2% contains 20 mg of erythromycin.

Each pledget is supplied in an individual foil packet in boxes of 60.

NDC 54868-0946-0.

Store at 20°- 25°C (68°- 77°F)[See USP Controlled Room Temperature].

E. FOUGERA & CO.
a division of Altana Inc.
MELVILLE, NY 11747

IF221501
R6/06
#46

Relabeling of "Additional Barcode Label" by:
Physicians Total Care, Inc.
Tulsa, OK 74146

PATIENT COUNSELING INFORMATION

Remove this portion before dispensing

ERYTHROMYCIN PLEDGETS, USP

Patient Information Leaflet

1. This medication is to be used as directed by the physician. It is for external use only. Avoid contact with the eyes, nose, mouth, and all mucous membranes.
2. This medication should not be used for any disorder other than that for which it was prescribed.
3. Patients should not use any other topical acne medication unless otherwise directed by their physician.
4. Patients should report to their physician any signs of local adverse reactions.

E. FOUGERA & CO.
a division of Altana Inc.
MELVILLE, NEW YORK 11747

PRINCIPAL DISPLAY PANEL

Erythromycin Topical Solution USP 2%